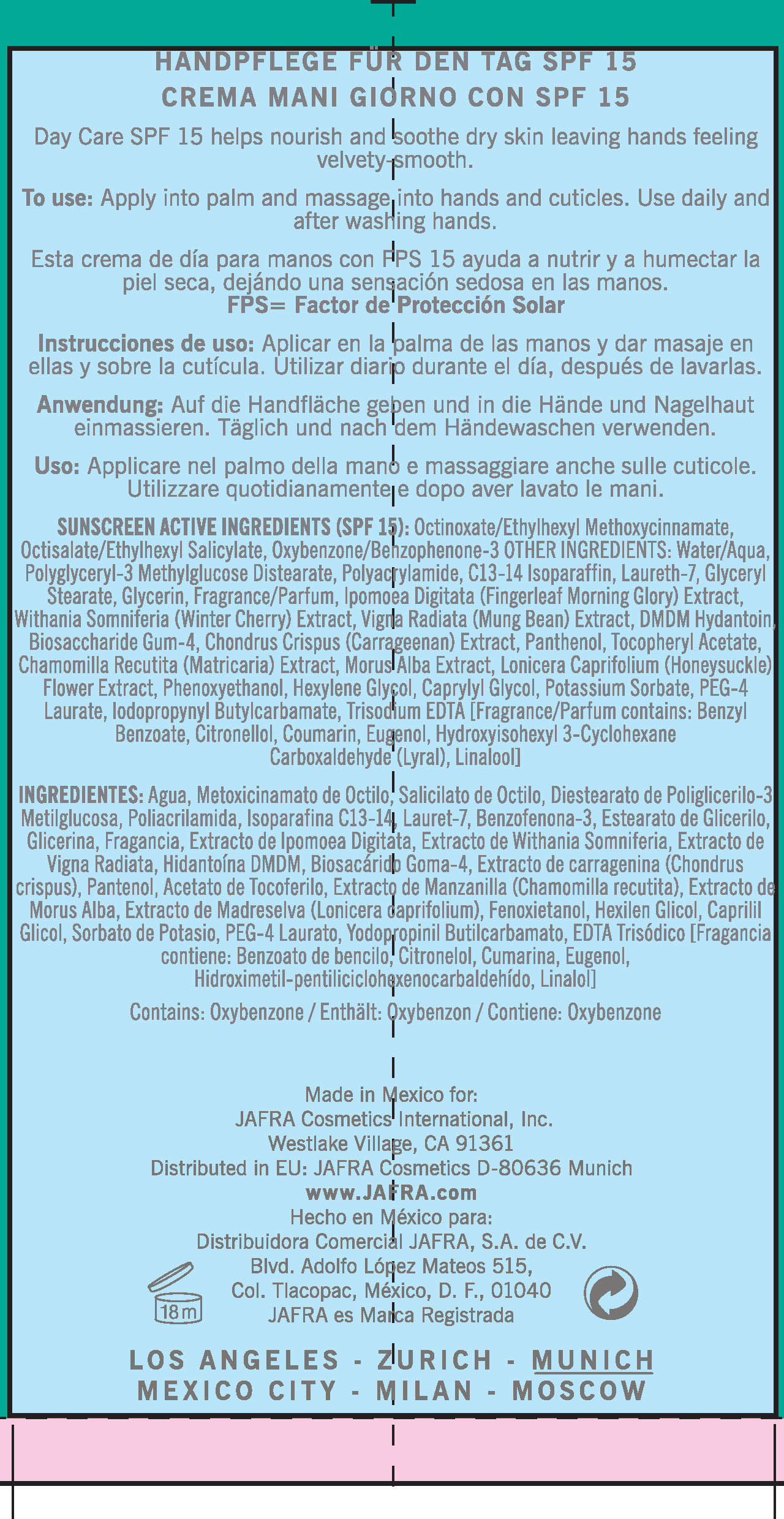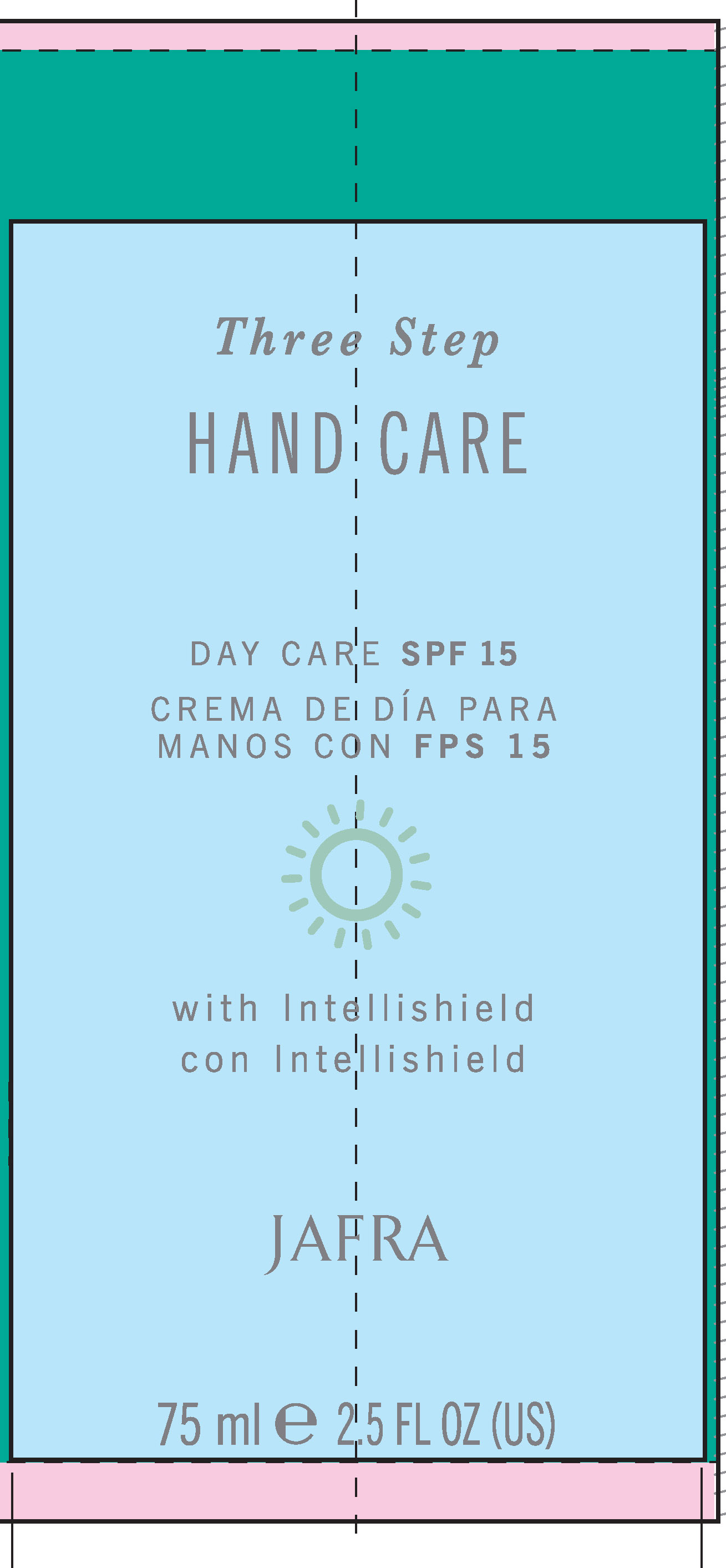 DRUG LABEL: Three step hand care
NDC: 68828-093 | Form: CREAM
Manufacturer: JAFRA COSMETICS INTERNATIONAL
Category: otc | Type: HUMAN OTC DRUG LABEL
Date: 20190523

ACTIVE INGREDIENTS: OCTINOXATE 7.5 g/100 mL; OCTISALATE 4 g/100 mL; OXYBENZONE 2 g/100 mL
INACTIVE INGREDIENTS: WATER; POLYACRYLIC ACID (250000 MW); C13-14 ISOPARAFFIN; LAURETH-7; GLYCERYL MONOSTEARATE; GLYCERIN; MUNG BEAN; DMDM HYDANTOIN; CHONDRUS CRISPUS; PANTHENOL; .ALPHA.-TOCOPHEROL ACETATE; MATRICARIA RECUTITA; MORUS ALBA BARK; LONICERA CAPRIFOLIUM FLOWER; PHENOXYETHANOL; HEXYLENE GLYCOL; CAPRYLYL GLYCOL; POTASSIUM SORBATE; PEG-4 LAURATE; IODOPROPYNYL BUTYLCARBAMATE; EDETATE TRISODIUM

Three Step Hand Care

ACTIVE INGREDIENT

Sunscreen Active Ingredients (SPF 15) : Octinoxate/Ethylhexylmethoxycinnamate, Octisalate/Ethylhexyl Salicylate, Oxybenzone/Benzophenone-3

PURPOSE

Day care SPF 15 helps nourish and soothe dry skin leaving hands feeling velvety smooth.

KEEP OUT OF REACH OF CHILDREN

No such information

INDICATIONS AND USAGE

To use Apply into palm and massage into hands and cuticles. Use daily and after washing hands.

WARNINGS

Anwendung: Auf Die Handfandflache geben und in die hande und Nagelhaut einmassieren, Taglich und nach dem handewaschen verwenden.

DOSAGE AND ADMINISTRATION

To use: Apply into palm and massage into hands and cuticles. Use daily and after washing hands.

INACTIVE INGREDIENT

Other ingredients: Water/Aqua, Polyglyceryl-3 Methylglucose Distearate, Polyacrylamide , C13-14 Isoparaffin , Laureth-7, Glyceryl Stearate,Glycerin, Fragrance/Parfum, Ipomoea Digitata (Fingerleaf Morning Glory) Extract, Withania Somnifera (winter Cherry) Extract, Vigna Radiata (Mung bean) Extract, DMDM Hydantoin, Biosaccharide Gum-4, Chondrus Chrispus (carrageenan) Extract, Panthenol, Tocopheryl Acetate, Chamomilla Recutita (Matricaria) Extract, Morus Alba Extract, Lonicera Caprifolium (Honeysuckle) Flower Extract, Phenoxyethanol, Hexylene Glycol, Caprylyl Glycol, Potassium Sorbate, PEG-4 Laurate, Iodoproynyl Butylcarbamate , Trisodium EDTA [fragrance/parfum contains: Benzyl Benzoate, Citronellol, Coumarin, Eugenol, Hydroxyisohexyl 3-cyclohexane Carboxaldehyde (Lyral) Linalool]

PACKAGE LABEL

Three Step

Hand Care
Day Care SPF 15
Crema De Dia Para Manos Con FPS 15

Jafra

75 ml 2.5 Fl Oz (US)